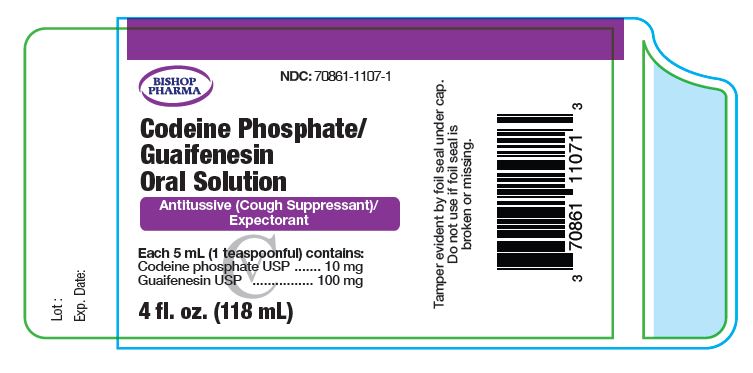 DRUG LABEL: Codeine Phosphate and Guaifenesin
NDC: 70861-1107 | Form: LIQUID
Manufacturer: Bishop Pharma, LLC
Category: otc | Type: HUMAN OTC DRUG LABEL
Date: 20200121
DEA Schedule: CV

ACTIVE INGREDIENTS: CODEINE PHOSPHATE 10 mg/5 mL; GUAIFENESIN 100 mg/5 mL
INACTIVE INGREDIENTS: CITRIC ACID MONOHYDRATE; EDETATE DISODIUM; FD&C RED NO. 40; GLYCERIN; MALTODEXTRIN; PROPYLENE GLYCOL; WATER; SODIUM BENZOATE; TRISODIUM CITRATE DIHYDRATE; SORBITOL; SUCRALOSE

Codeine Phosphate and Guaifenesin
CV

Active ingredients (in each teaspoonful (5 mL))

Codeine phosphate USP 10 mg

Guaifenesin USP 100 mg

Purpose

Antitussive (Cough Suppressant)

Expectorant

Uses

- temporarily relieves cough due to minor throat and bronchial irritation as may occur with a cold or inhaled irritants
- relieves your cough to help you sleep
- helps loosen phlegm (mucus) and thin bronchial secretions to rid the bronchial passageways of bothersome mucus and make coughs more productive
- temporarily relieves cough associated with the common cold

Ask your Doctor if:

- you have a persistent or chronic cough, this may be a sign of a serious condition
- you have a persistent or chronic cough such as occurs with smoking, asthma, chronic bronchitis or emphysema
- you have a cough that is accompanied by excessive phlegm (mucus)
- you have chronic pulmonary disease or shortness of breath
- giving to a child who is taking other drugs

When using this product

- giving a higher dose than recommended by a doctor could result in serious side effects for your child. A special measuring device should be used to give an accurate dose of this product to children under 6 years of age
- may cause or aggravate constipation

Stop use and ask a doctor if

- symptoms do not improve within 7 days, tend to recur or are accompanied by fever, rash, or persistent headache. These may be symptoms of a serious condition.

PREGNANCY OR BREAST FEEDING

If pregnant or breast-feeding, ask a health professional before use.

Keep out of reach of children.

In case of overdose, get medical help or contact a Poison Control Center right away.

Directions

- do not exceed 6 doses in 24 hours

Adults and children 12 years of age and over: | 2 tsp (10 mL) every 4 hours, or as directed by a doctor.
Children 6 to under 12 years of age: | 1 tsp (5 mL) every 4 hours, or as directed by a doctor.
Children under 6 years of age: | Consult a doctor.

Other information

Store at controlled room temperature 20° to 25°C (68° to 77°F)

Inactive ingredients

Cherry flavor, citric acid, ededate disodium, FD&C red #40, glycerin, maltodextrin, propylene glycol, purified water, sodium benzoate, sodium citrate dihydrate, sorbitol, sucralose

Question or Comments
Please call 1-888-514-4727

Marketed by: Bishop Pharma, LLC
Pompano, FL 33069